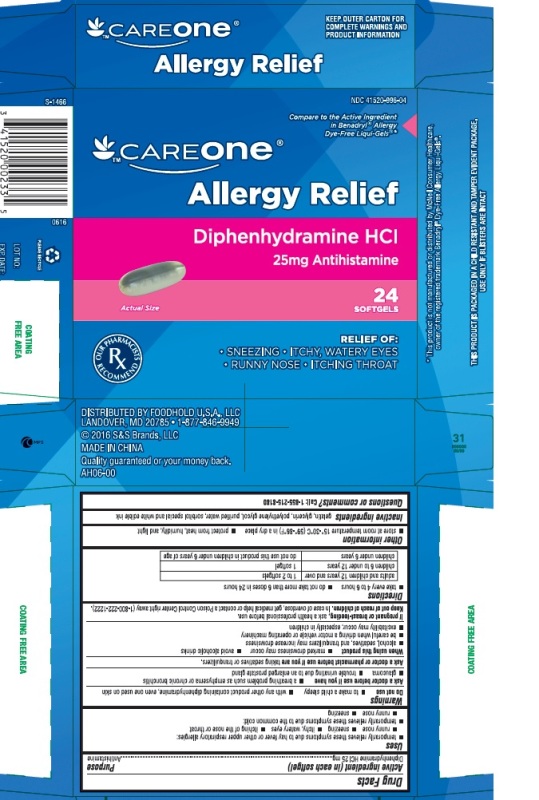 DRUG LABEL: Allergy Relief
NDC: 41520-996 | Form: CAPSULE, LIQUID FILLED
Manufacturer: FOODHOLD U.S.A., LLC
Category: otc | Type: HUMAN OTC DRUG LABEL
Date: 20241124

ACTIVE INGREDIENTS: DIPHENHYDRAMINE HYDROCHLORIDE 25 mg/1 1
INACTIVE INGREDIENTS: GELATIN; GLYCERIN; POLYETHYLENE GLYCOL, UNSPECIFIED; WATER; SORBITOL

Allergy Relief

Drug Facts

Active ingredient (in each softgel)

Diphenhydramine HCl 25 mg

Purpose

Antihistamine

Uses

- temporarily relieves these symptoms due to hay fever or other upper respiratory allergies:
  - runny nose
  - sneezing
  - itchy, watery eyes
  - itching of the nose or throat
- temporarily relieves these symptoms due to the common cold:
  - runny nose
  - sneezing

Warnings

Do not use

- to make a child sleepy
- with any other product containing diphenhydramine, even one used on skin

Ask a doctor before use if you have

- a breathing problem such as emphysema or chronic bronchitis
- glaucoma
- trouble urinating due to an enlarged prostate gland

Ask a doctor or pharmacist before use if you aretaking sedatives or tranquilizers.

When using this product

- marked drowsiness may occur
- avoid alcoholic drinks
- alcohol, sedatives, and tranquilizers may increase drowsiness
- be careful when driving a motor vehicle or operating machinery
- excitability may occur, especially in children

PREGNANCY OR BREAST FEEDING

If pregnant or breast-feeding,ask a health professional before use.

Keep out of reach of children.

In case of overdose, get medical help or contact a Poison Control Center right away (1-800-222-1222).

Directions

- take every 4 to 6 hours
- do not take more than 6 doses in 24 hours

adults and children 12 years and over | 1 to 2 softgels
children 6 to under 12 years | 1 softgel
children under 6 years | do not use this product in children under 6 years of age

Other information

- store at room temperature 15°-30°C (59°-86°F) in a dry place
- protect from heat, humidity, and light

Inactive ingredients

gelatin, glycerin, polyethylene glycol, purified water, sorbitol special and white edible ink

Questions or comments?

Call:1-855-215-8180

PRINCIPAL DISPLAY PANEL - Carton Label

CAREONE Allergy Relief

Diphenhydramine HCl 25 mg 24 softgels

NDC 41520-996-04

*Compare to the active ingredient in Benadryl®Dye-Free Allergy Liqui-Gels®